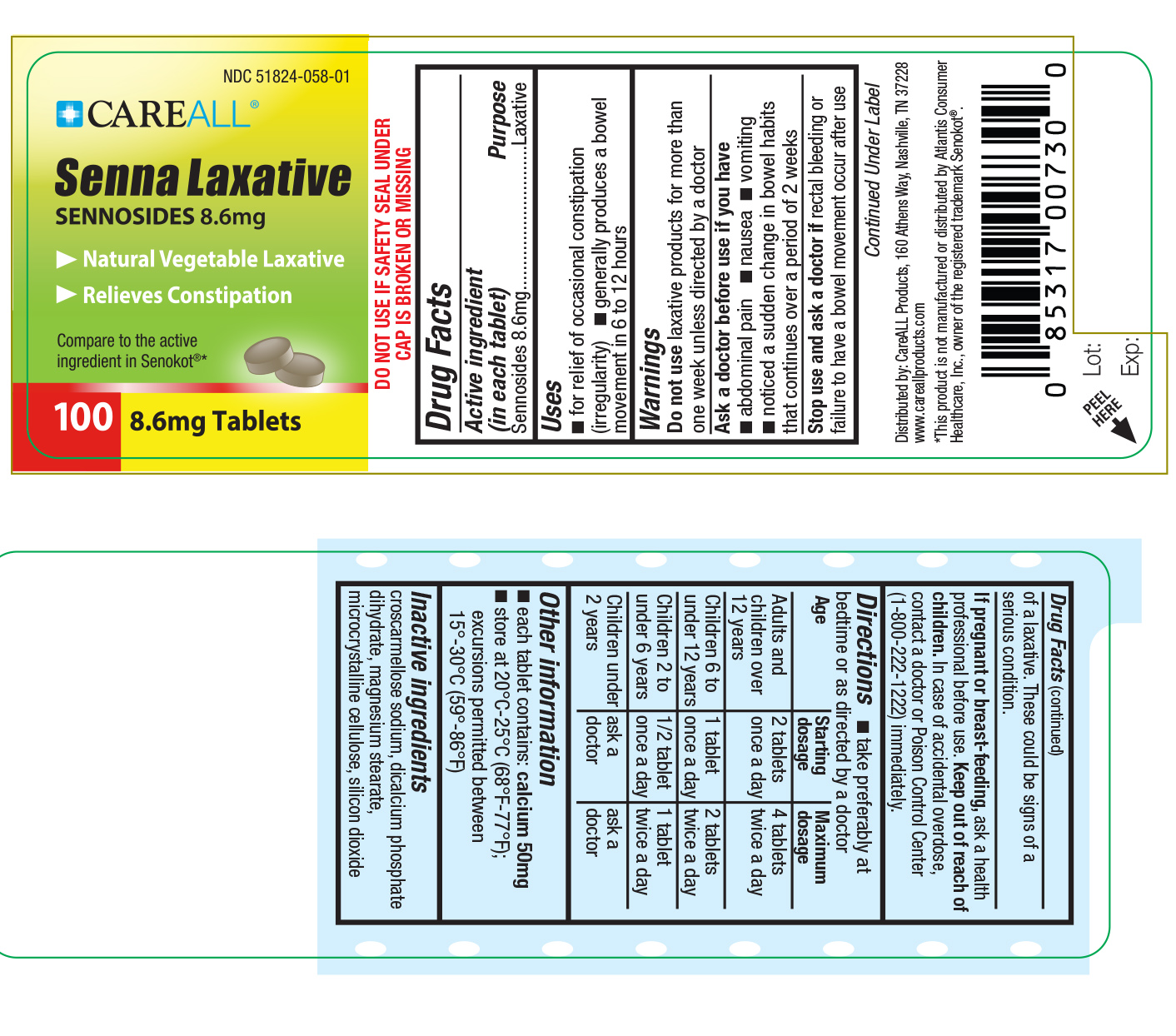 DRUG LABEL: CAREALL Sennosides
NDC: 51824-058 | Form: TABLET
Manufacturer: New World Imports, Inc
Category: otc | Type: HUMAN OTC DRUG LABEL
Date: 20251222

ACTIVE INGREDIENTS: SENNOSIDES A AND B 8.6 mg/1 1
INACTIVE INGREDIENTS: SILICON DIOXIDE; CROSCARMELLOSE SODIUM; DIBASIC CALCIUM PHOSPHATE DIHYDRATE; MAGNESIUM STEARATE; CELLULOSE, MICROCRYSTALLINE

Drug Facts

Active Ingredient

Sennosides

Purpose

Laxative

Keep out of Reach of Children

In case of accidental overdose, contact a doctor or Poison Control Center immediately.

Uses

For relief of occasional constipation and irregularity.

This product produces a bowel movement in 6 to 12 hours.

Warnings

Do not use laxative products for more than one week unless directed by a doctor

Ask a doctor before use if you have stomach pains, nausea, vomiting, notice a sudden change in bowel habits that continues over a period of 2 weeks.

Stop use and ask a doctor ifrectal bleeding or failure to have a bowel movement occur after use of a laxative. These could be signs of a serious condition.

If Pregnant or breast-feedingask a health professional before use.

Directions

Take preferably at bedtime or as directed by a doctor.

Adults and children over 12 years: 2 tablets once a day. Maximum of 4 tablets twice a day.

Children 6 to under 12 years: 1 tablet once a day. Maximum of 2 tablets twice a day.

Children 2 to under 6 years: 1/2 tablet once a day. Maximum of 1 tablet twice a day.

Children under 2: consult a doctor

Inactive Ingredients

croscarmellose sodium, dibasic dicalcium phosphate, magnesium stearate, microcrystalline cellulose, and silicon dioxide.